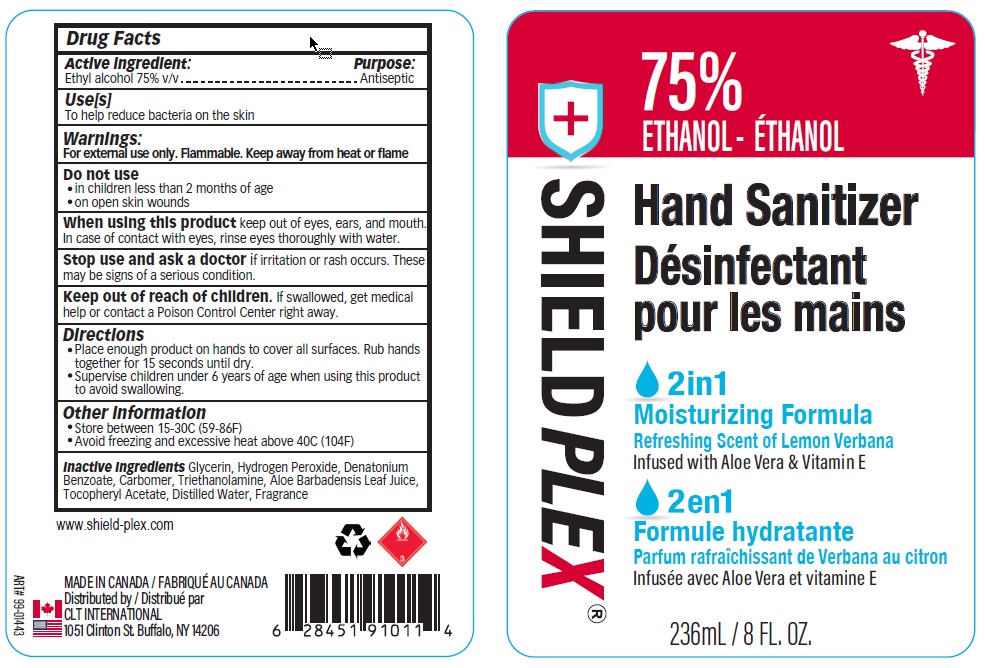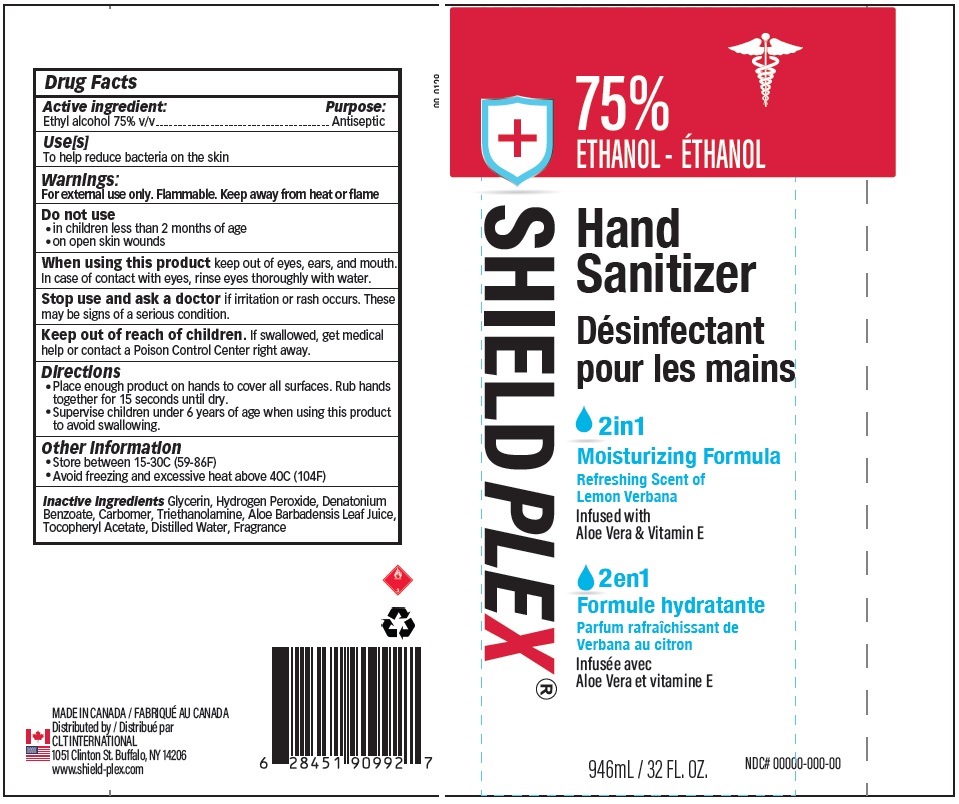 DRUG LABEL: Shieldplex Hand Sanitizer
NDC: 75490-007 | Form: GEL
Manufacturer: CLT Logistics, Inc
Category: otc | Type: HUMAN OTC DRUG LABEL
Date: 20200802

ACTIVE INGREDIENTS: ALCOHOL 75 mL/100 mL
INACTIVE INGREDIENTS: GLYCERIN; HYDROGEN PEROXIDE; DENATONIUM BENZOATE; CARBOMER HOMOPOLYMER, UNSPECIFIED TYPE; TROLAMINE; .ALPHA.-TOCOPHEROL ACETATE; ALOE VERA LEAF; WATER

Active Ingredient

Ethyl alcohol 75% v/v.

Purpose

Antiseptic

Use

To help reduce bacteria on the skin.

Warnings

For external use only.

Flammable. Keep away from heat or flame.

Do not use

- in children less than 2 months of age
- on open skin wounds

When using this product keep out of eyes, ears, and mouth. In case of contact with eyes, rinse eyes thoroughly with water.

Stop use and ask a doctor if irritation or rash occurs. These may be signs of a serious condition.

Keep out of reach of children. If swallowed, get medical help or contact a Poison Control Center right away.

Directions

Place enough product on hands to cover all surfaces. Rub hands together for 15 seconds until dry.
Supervise children under 6 years of age when using this product to avoid swallowing.

Other information

- Store between 15-30C (59-86F)
- Avoid freezing and excessive heat above 40C (104F)

Inactive ingredients

Glycerin, Hydrogen Peroxide, Denatonium Benzoate, Carbomer, Triethanolamine, Aloe Barbadensis Leaf Juice, Tocopheryl Acetate, Distilled Water, Fragrance.